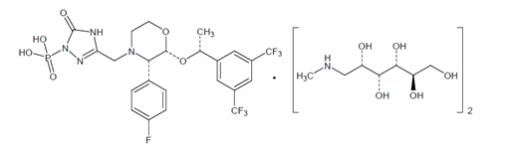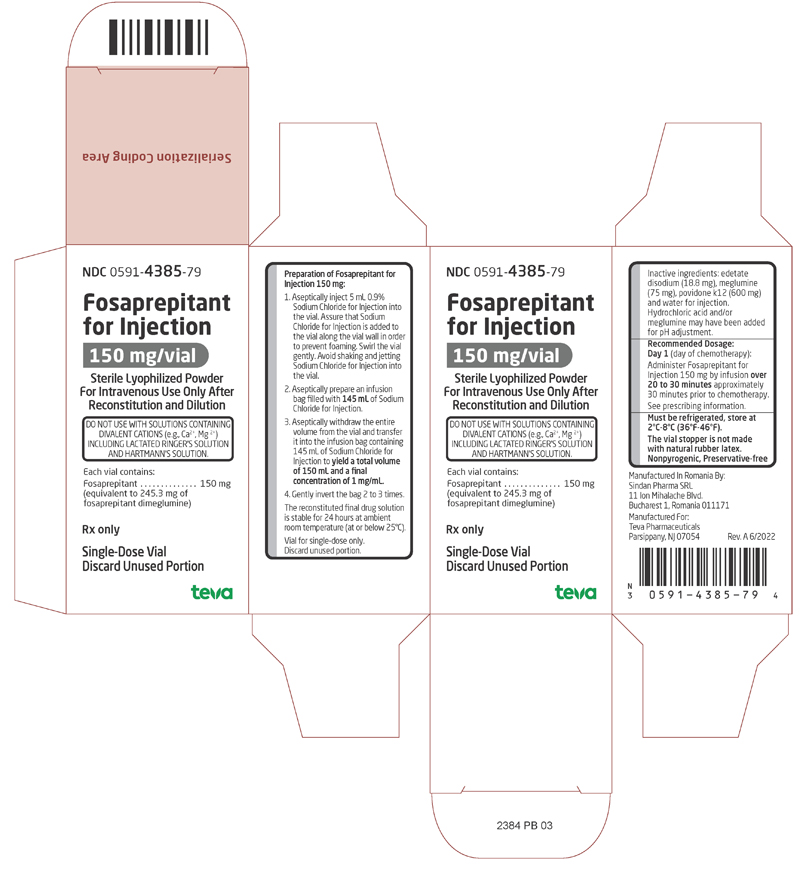 DRUG LABEL: Fosaprepitant
NDC: 0591-4385 | Form: INJECTION, POWDER, LYOPHILIZED, FOR SOLUTION
Manufacturer: Actavis Pharma, Inc.
Category: prescription | Type: HUMAN PRESCRIPTION DRUG LABEL
Date: 20220630

ACTIVE INGREDIENTS: FOSAPREPITANT DIMEGLUMINE 150 mg/1 1
INACTIVE INGREDIENTS: EDETATE DISODIUM; MEGLUMINE; POVIDONE K12; WATER; HYDROCHLORIC ACID

HIGHLIGHTS OF PRESCRIBING INFORMATION

These highlights do not include all the information needed to use FOSAPREPITANT FOR INJECTION safely and effectively. See full prescribing information for FOSAPREPITANT FOR INJECTION.
FOSAPREPITANT for injection, for intravenous use
Initial U.S. Approval: 2008

1 INDICATIONS AND USAGE

Fosaprepitant for Injection is a substance P/neurokinin-1 (NK1) receptor antagonist, indicated in adults, in combination with other antiemetic agents, for the prevention of (1):

- acute and delayed nausea and vomiting associated with initial and repeat courses of highly emetogenic cancer chemotherapy (HEC) including high-dose cisplatin.
- delayed nausea and vomiting associated with initial and repeat courses of moderately emetogenic cancer chemotherapy (MEC).

Limitations of Use (1)

- Fosaprepitant for Injection has not been studied for treatment of established nausea and vomiting.

2 DOSAGE AND ADMINISTRATION

Dosage (2.1)

- The recommended dosage in adults is 150 mg on Day 1 as an intravenous infusion over 20 to 30 minutes completing the infusion approximately 30 minutes prior to chemotherapy.
- See Full Prescribing Information for dosages of concomitant antiemetic(s) of Fosaprepitant for Injection.

Preparation (2.2)

- Reconstitute with 5 mL of 0.9% sodium chloride.
- Add to infusion bag containing 145 mL 0.9% sodium chloride for a final concentration of 1 mg/mL.

3 DOSAGE FORMS AND STRENGTHS

Fosaprepitant for Injection: 150 mg fosaprepitant, lyophilized powder in single-dose vial for reconstitution. (3)

4 CONTRAINDICATIONS

- Known hypersensitivity to any component of this drug. (4, 5.2)
- Concurrent use with pimozide. (4)

5 WARNINGS AND PRECAUTIONS

- CYP3A4 Interactions: Fosaprepitant is a weak inhibitor of CYP3A4, and aprepitant, the active moiety, is a substrate, inhibitor, and inducer of CYP3A4; see Full Prescribing Information for recommendations regarding contraindications, risk of adverse reactions, and dosage adjustment of Fosaprepitant for Injection and concomitant drugs. (4, 5.1, 7.1, 7.2)
- Hypersensitivity Reactions (including anaphylaxis and anaphylactic shock): May occur during or soon after infusion. If symptoms occur, discontinue the drug. Do not reinitiate Fosaprepitant for Injection if symptoms occur with previous use. (4, 5.2)
- Infusion Site Reactions (including thrombophlebitis, necrosis, and vasculitis): Majority of reactions reported in patients receiving vesicant chemotherapy. Avoid infusion into small veins. Discontinue infusion and administer treatment if a severe reaction develops. (5.3)
- Warfarin (a CYP2C9 substrate): Risk of decreased INR of prothrombin time; monitor INR in 2-week period, particularly at 7 to 10 days, following initiation of Fosaprepitant for Injection. (5.4, 7.1)
- Hormonal Contraceptives: Efficacy of contraceptives may be reduced during and for 28 days following administration of Fosaprepitant for Injection. Use effective alternative or back-up methods of contraception. (5.5, 7.1, 8.3)

6 ADVERSE REACTIONS

- Most common adverse reactions (≥2%) are: fatigue, diarrhea, neutropenia, asthenia, anemia, peripheral neuropathy, leukopenia, dyspepsia, urinary tract infection, pain in extremity. (6.1)

To report SUSPECTED ADVERSE REACTIONS, contact Teva 1-888-838-2872 or FDA at 1-800-FDA-1088 or www.fda.gov/medwatch.

7 DRUG INTERACTIONS

See Full Prescribing Information for a list of clinically significant drug interactions. (4, 5.1, 5.4, 5.5, 7.1, 7.2)

FULL PRESCRIBING INFORMATION

1 INDICATIONS AND USAGE

Fosaprepitant for Injection, in combination with other antiemetic agents, is indicated in adults for the prevention of:

- acute and delayed nausea and vomiting associated with initial and repeat courses of highly emetogenic cancer chemotherapy (HEC) including high-dose cisplatin.
- delayed nausea and vomiting associated with initial and repeat courses of moderately emetogenic cancer chemotherapy (MEC).

Limitations of Use

- Fosaprepitant for Injection has not been studied for the treatment of established nausea and vomiting.

2 DOSAGE AND ADMINISTRATION

2.1 Recommended Dosage

The recommended dosage of Fosaprepitant for Injection, dexamethasone, and a 5-HT3 antagonist for the prevention of nausea and vomiting associated with administration of HEC or MEC in adults is shown in Table 1 or Table 2, respectively. Administer Fosaprepitant for Injection as an intravenous infusion on Day 1 over 20 to 30 minutes, completing the infusion approximately 30 minutes prior to chemotherapy.

Table 1 Recommended Dosage for the Prevention of Nausea and Vomiting Associated with HEC
 | Day 1 | Day 2 | Day 3 | Day 4
Fosaprepitant for Injection | 150 mg intravenously over 20 to 30 minutes | none | none | none
Dexamethasone* | 12 mg orally | 8 mg orally | 8 mg orally twice daily | 8 mg orally twice daily
5-HT3 antagonist | See selected 5-HT3 antagonist prescribing information for the recommended dosage | none | none | none
*Administer dexamethasone 30 minutes prior to chemotherapy treatment on Day 1 and in the morning on Days 2 through 4. Also administer dexamethasone in the evenings on Days 3 and 4. A 50% dosage reduction of dexamethasone on Days 1 and 2 is recommended to account for a drug interaction with Fosaprepitant for Injection [see Clinical Pharmacology (12.3)].

Table 2 Recommended Dosage for the Prevention of Nausea and Vomiting Associated with MEC
 | Day 1
Fosaprepitant for Injection | 150 mg intravenously over 20 to 30 minutes
Dexamethasone* | 12 mg orally
5-HT3 antagonist | See selected 5-HT3 antagonist prescribing information for the recommended dosage
*Administer dexamethasone 30 minutes prior to chemotherapy treatment on Day 1. A 50% dosage reduction of dexamethasone is recommended to account for a drug interaction with Fosaprepitant for Injection [see Clinical Pharmacology (12.3)].

2.2 Preparation Instructions

Table 5 Preparation Instructions for Fosaprepitant for Injection (150 mg)
Step 1 | Aseptically inject 5 mL 0.9% Sodium Chloride Injection, USP into the vial. Assure that 0.9% Sodium Chloride Injection, USP is added to the vial along the vial wall in order to prevent foaming. Swirl the vial gently. Avoid shaking and jetting 0.9% Sodium Chloride Injection, USP into the vial.
Step 2 | Aseptically prepare an infusion bag filled with 145 mL of 0.9% Sodium Chloride Injection, USP.
Step 3 | Aseptically withdraw the entire volume from the vial and transfer it into the infusion bag containing 145 mL of 0.9% Sodium Chloride Injection, USP to yield a total volume of 150 mL and a final concentration of 1 mg/mL.
Step 4 | Gently invert the bag 2 to 3 times.
Step 5 | Before administration, inspect the bag for particulate matter and discoloration. Discard the bag if particulate and/or discoloration are observed.

Caution: Do not mix or reconstitute Fosaprepitant for Injection with solutions for which physical and chemical compatibility have not been established. Fosaprepitant for Injection is incompatible with any solutions containing divalent cations (e.g., calcium, magnesium), including Lactated Ringer’s Solution and Hartmann's Solution.

Storage

The reconstituted final drug solution is stable for 24 hours at ambient room temperature [at or below 25°C (77°F)].

3 DOSAGE FORMS AND STRENGTHS

Fosaprepitant for Injection: 150 mg fosaprepitant, white to off-white lyophilized powder in single-dose glass vial for reconstitution

4 CONTRAINDICATIONS

Fosaprepitant for Injection is contraindicated in patients:

- who are hypersensitive to any component of the product. Hypersensitivity reactions including anaphylactic reactions, flushing, erythema, and dyspnea have been reported [see Warnings and Precautions (5.2), Adverse Reactions (6.2)].
- taking pimozide. Inhibition of CYP3A4 by aprepitant, the active moiety, could result in elevated plasma concentrations of this drug, which is a CYP3A4 substrate, potentially causing serious or life-threatening reactions, such as QT prolongation, a known adverse reaction of pimozide [see Warnings and Precautions (5.1)].

5 WARNINGS AND PRECAUTIONS

5.1 Clinically Significant CYP3A4 Drug Interactions

Fosaprepitant, a prodrug of aprepitant, is a weak inhibitor of CYP3A4, and aprepitant is a substrate, inhibitor, and inducer of CYP3A4.

- Use of Fosaprepitant for Injection with other drugs that are CYP3A4 substrates, may result in increased plasma concentration of the concomitant drug.
  - Use of pimozide with Fosaprepitant for Injection is contraindicated due to the risk of significantly increased plasma concentrations of pimozide, potentially resulting in prolongation of the QT interval, a known adverse reaction of pimozide [see Contraindications (4)].
- Use of Fosaprepitant for Injection with strong or moderate CYP3A4 inhibitors (e.g., ketoconazole, diltiazem) may increase plasma concentrations of aprepitant and result in an increased risk of adverse reactions related to Fosaprepitant for Injection.
- Use of Fosaprepitant for Injection with strong CYP3A4 inducers (e.g., rifampin) may result in a reduction in aprepitant plasma concentrations and decreased efficacy of Fosaprepitant for Injection.

See Table 7 and Table 8 for a listing of potentially significant drug interactions [see Drug Interactions (7.1, 7.2)].

5.2 Hypersensitivity Reactions

Serious hypersensitivity reactions, including anaphylaxis and anaphylactic shock, during or soon after infusion of fosaprepitant have occurred. Symptoms including flushing, erythema, dyspnea, hypotension and syncope have been reported [see Adverse Reactions (6.2)].

Monitor patients during and after infusion. If hypersensitivity reactions occur, discontinue the infusion and administer appropriate medical therapy. Do not reinitiate Fosaprepitant for Injection in patients who experience these symptoms with previous use [see Contraindications (4)].

5.3 Infusion Site Reactions

Infusion site reactions (ISRs) have been reported with the use of Fosaprepitant for Injection [see Adverse Reactions (6.1)]. The majority of severe ISRs, including thrombophlebitis and vasculitis, were reported with concomitant vesicant (anthracycline-based) chemotherapy administration, particularly when associated with extravasation. Necrosis was also reported in some patients with concomitant vesicant chemotherapy. Most ISRs occurred with the first, second or third exposure to single doses of Fosaprepitant for Injection and in some cases, reactions persisted for two weeks or longer. Treatment of severe ISRs consisted of medical, and in some cases surgical, intervention.

Avoid infusion of Fosaprepitant for Injection into small veins or through a butterfly catheter. If a severe ISR develops during infusion, discontinue the infusion and administer appropriate medical treatment.

5.4 Decrease in INR with Concomitant Warfarin

Coadministration of Fosaprepitant for Injection with warfarin, a CYP2C9 substrate, may result in a clinically significant decrease in the International Normalized Ratio (INR) of prothrombin time [see Clinical Pharmacology (12.3)]. Monitor the INR in patients on chronic warfarin therapy in the 2-week period, particularly at 7 to 10 days, following initiation of Fosaprepitant for Injection with each chemotherapy cycle [see Drug Interactions (7.1)].

5.5 Risk of Reduced Efficacy of Hormonal Contraceptives

Upon coadministration with Fosaprepitant for Injection, the efficacy of hormonal contraceptives may be reduced during administration of and for 28 days following the last dose of Fosaprepitant for Injection [see Clinical Pharmacology (12.3)]. Advise patients to use effective alternative or back-up methods of contraception during treatment with Fosaprepitant for Injection and for 1 month following administration of Fosaprepitant for Injection [see Drug Interactions (7.1), Use in Specific Populations (8.3)].

6 ADVERSE REACTIONS

The following clinically significant adverse reactions are described elsewhere in the labeling:

- Hypersensitivity Reactions [see Warnings and Precautions (5.2)]
- Infusion Site Reactions [see Warnings and Precautions (5.3)]

6.1 Clinical Trials Experience

Because clinical trials are conducted under widely varying conditions, adverse reaction rates observed in the clinical trials of a drug cannot be directly compared to rates in the clinical trials of another drug and may not reflect the rates observed in clinical practice.

The safety of Fosaprepitant for Injection has been established from adequate and well-controlled studies of another intravenous fosaprepitant product in chemotherapy induced nausea and vomiting [see Clinical Studies (14)]. Adverse reactions reported in these studies are described below.

Adverse Reactions for the Prevention of Nausea and Vomiting Associated with MEC

In an active-controlled clinical trial in patients receiving MEC, safety was evaluated in 504 adult patients receiving a single intravenous dose of fosaprepitant in combination with ondansetron and dexamethasone (fosaprepitant regimen) compared to 497 patients receiving ondansetron and dexamethasone alone (standard therapy). The most common adverse reactions are listed in Table 6.

Table 6 Most Common Adverse Reactions in Patients Receiving MEC*
 | Intravenous fosaprepitant, ondansetron, and dexamethasone†; (N=504) | Ondansetron and dexamethasone‡; (N=497)
fatigue | 15% | 13%
diarrhea | 13% | 11%
neutropenia | 8% | 7%
asthenia | 4% | 3%
anemia | 3% | 2%
peripheral neuropathy | 3% | 2%
leukopenia | 2% | 1%
dyspepsia | 2% | 1%
urinary tract infection | 2% | 1%
pain in extremity | 2% | 1%
* Reported in ≥2% of patients treated with the fosaprepitant regimen and at a greater incidence than standard therapy.
†Fosaprepitant regimen
‡Standard therapy

Infusion-site reactions were reported in 2.2% of patients treated with the fosaprepitant regimen compared to 0.6% of patients treated with standard therapy. The infusion-site reactions included: infusion-site pain (1.2%, 0.4%), injection-site irritation (0.2%, 0.0%), vessel puncture-site pain (0.2%, 0.0%), and infusion-site thrombophlebitis (0.6%, 0.0%), reported in the fosaprepitant regimen compared to standard therapy, respectively.

Adverse Reactions for the Prevention of Nausea and Vomiting Associated with HEC

In an active-controlled clinical study in patients receiving HEC, safety was evaluated for 1143 adult patients receiving a single intravenous dose of fosaprepitant compared to 1169 patients receiving the 3-day regimen of oral aprepitant [see Clinical Studies (14.1)]. The safety profile was generally similar to that seen in the MEC study with fosaprepitant and prior HEC studies with aprepitant. However, infusion-site reactions occurred at a higher incidence in patients in the fosaprepitant group (3.0%) compared to those in the aprepitant group (0.5%). The following additional infusion-site reactions occurred in the HEC study and were not reported in the MEC study described above: infusion-site erythema (0.5%, 0.1%), infusion-site pruritus (0.3%, 0.0%), and infusion-site induration (0.2%, 0.1%), reported in the fosaprepitant group compared to the aprepitant group, respectively.

Because fosaprepitant is converted to aprepitant, those adverse reactions associated with aprepitant might also be expected to occur with Fosaprepitant for Injection. See the full prescribing information for aprepitant capsules for complete safety information regarding studies performed with oral aprepitant.

6.2 Postmarketing Experience

The following adverse reactions have been identified during post-approval use of another intravenous formulation of fosaprepitant. Because these reactions are reported voluntarily from a population of uncertain size, it is not always possible to reliably estimate their frequency or establish a causal relationship to drug exposure.

Skin and subcutaneous tissue disorders: pruritus, rash, urticaria, Stevens-Johnson syndrome/toxic epidermal necrolysis [see Warnings and Precautions (5.2)].

Immune system disorders: hypersensitivity reactions including anaphylaxis and anaphylactic shock [see Contraindications (4), Warnings and Precautions (5.2)].

Nervous system disorders: ifosfamide-induced neurotoxicity reported after fosaprepitant and ifosfamide coadministration.

7 DRUG INTERACTIONS

7.1 Effect of Fosaprepitant/Aprepitant on the Pharmacokinetics of Other Drugs

When administered intravenously, fosaprepitant, a prodrug of aprepitant, is converted to aprepitant within 30 minutes. Therefore, drug interactions following administration of Fosaprepitant for Injection are likely to occur with drugs that interact with oral aprepitant.

Fosaprepitant, given as a single 150-mg dose, is a weak inhibitor of CYP3A4, and the weak inhibition of CYP3A4 continues for 2 days after single dose administration. Single dose fosaprepitant does not induce CYP3A4. Aprepitant is a substrate, an inhibitor, and an inducer of CYP3A4. Aprepitant is also an inducer of CYP2C9 [see Clinical Pharmacology (12.3)].

Some substrates of CYP3A4 are contraindicated with Fosaprepitant for Injection [see Contraindications (4)]. Dosage adjustment of some CYP3A4 and CYP2C9 substrates may be warranted, as shown in Table 7.

Table 7 Effects of Fosaprepitant/Aprepitant on the Pharmacokinetics of Other Drugs
CYP3A4 Substrates
Pimozide
Clinical Impact | Increased pimozide exposure
Intervention | Fosaprepitant for Injection is contraindicated [see Contraindications (4)].
Benzodiazepines
Clinical Impact | Increased exposure to midazolam or other benzodiazepines metabolized via CYP3A4 (alprazolam, triazolam) may increase the risk of adverse reactions [see Clinical Pharmacology (12.3)].
Intervention | Monitor for benzodiazepine-related adverse reactions.
Dexamethasone
Clinical Impact | Increased dexamethasone exposure [see Clinical Pharmacology (12.3)].
Intervention | Reduce the dose of oral dexamethasone by approximately 50% [see Dosage and Administration (2.1)].
Methylprednisolone
Clinical Impact | Increased methylprednisolone exposure [see Clinical Pharmacology (12.3)].
Intervention | Reduce the dose of oral methylprednisolone by approximately 50% on Days 1 and 2 for patients receiving HEC and on Day 1 for patients receiving MEC.; Reduce the dose of intravenous methylprednisolone by 25% on Days 1 and 2 for patients receiving HEC and on Day 1 for patients receiving MEC.
Chemotherapeutic agents that are metabolized by CYP3A4
Clinical Impact | Increased exposure of the chemotherapeutic agent may increase the risk of adverse reactions [see Clinical Pharmacology (12.3)].
Intervention | Vinblastine, vincristine, or ifosfamide or other chemotherapeutic agents; - Monitor for chemotherapeutic-related adverse reactions.; Etoposide, vinorelbine, paclitaxel, and docetaxel; - No dosage adjustment needed.
Hormonal Contraceptives
Clinical Impact | Decreased hormonal exposure during administration of and for 28 days after administration of the last dose of Fosaprepitant for Injection [see Warnings and Precautions (5.5), Use in Specific Populations (8.3), Clinical Pharmacology (12.3)].
Intervention | Effective alternative or back-up methods of contraception (such as condoms or spermicides) should be used during treatment with Fosaprepitant for Injection and for 1 month following administration of Fosaprepitant for Injection.
Examples | birth control pills, skin patches, implants, and certain IUDs
CYP2C9 Substrates
Warfarin
Clinical Impact | Decreased warfarin exposure and decreased prothrombin time (INR) [see Warnings and Precautions (5.4), Clinical Pharmacology (12.3)].
Intervention | In patients on chronic warfarin therapy, monitor the prothrombin time (INR) in the 2-week period, particularly at 7 to 10 days, following administration of Fosaprepitant for Injection with each chemotherapy cycle.
Other
5-HT3 Antagonists
Clinical Impact | No change in the exposure of the 5-HT3 antagonist [see Clinical Pharmacology (12.3)].
Intervention | No dosage adjustment needed
Examples | ondansetron, granisetron, dolasetron

7.2 Effect of Other Drugs on the Pharmacokinetics of Fosaprepitant/Aprepitant

Aprepitant is a CYP3A4 substrate [see Clinical Pharmacology (12.3)]. Coadministration of Fosaprepitant for Injection with drugs that are inhibitors or inducers of CYP3A4 may result in increased or decreased plasma concentrations of aprepitant, respectively, as shown in Table 8.

Table 8 Effects of Other Drugs on Pharmacokinetics of Fosaprepitant/Aprepitant
Moderate to Strong CYP3A4 Inhibitors
Clinical Impact | Significantly increased exposure of aprepitant may increase the risk of adverse reactions associated with Fosaprepitant for Injection [see Adverse Reactions (6.1), Clinical Pharmacology (12.3)].
Intervention | Avoid concomitant use of Fosaprepitant for Injection
Examples | Moderate inhibitor: diltiazem Strong inhibitors:; ketoconazole, itraconazole, nefazodone, troleandomycin, clarithromycin, ritonavir, nelfinavir
Strong CYP3A4 Inducers
Clinical Impact | Substantially decreased exposure of aprepitant in patients chronically taking a strong CYP3A4 inducer may decrease the efficacy of Fosaprepitant for Injection [see Clinical Pharmacology (12.3)].
Intervention | Avoid concomitant use of Fosaprepitant for Injection
Examples | rifampin, carbamazepine, phenytoin

8 USE IN SPECIFIC POPULATIONS

8.1 Pregnancy

Risk Summary

There are no available data on use of fosaprepitant in pregnant women to inform a drug-associated risk of adverse developmental outcomes. In animal reproduction studies, no adverse developmental effects were observed in rats or rabbits exposed during the period of organogenesis to systemic exposures (AUC) approximately equivalent to the exposure at the recommended human dose (RHD) of 150 mg [see Data].

The estimated background risk of major birth defects and miscarriage for the indicated populations is unknown. All pregnancies have a background risk of birth defect, loss, or other adverse outcomes. In the U.S. general population, the estimated background risk of major birth defects and miscarriage in clinically recognized pregnancies is 2% to 4% and 15% to 20%, respectively.

Data

Animal Data

In embryofetal development studies in rats and rabbits, aprepitant was administered during the period of organogenesis at oral doses up to 1,000 mg/kg twice daily (rats) and up to the maximum tolerated dose of 25 mg/kg/day (rabbits). No embryofetal lethality or malformations were observed at any dose level in either species. The exposures (AUC) in pregnant rats at 1,000 mg/kg twice daily and in pregnant rabbits at 25 mg/kg/day were approximately equivalent to the exposure at the RHD of 150 mg. Aprepitant crosses the placenta in rats and rabbits.

8.2 Lactation

Risk Summary

There are no data on the presence of aprepitant in human milk, the effects on the breastfed infant, or the effects on milk production. Aprepitant is present in rat milk. The developmental and health benefits of breastfeeding should be considered along with the mother’s clinical need for Fosaprepitant for Injection and any potential adverse effects on the breastfed infant from Fosaprepitant for Injection or from the underlying maternal condition.

8.3 Females and Males of Reproductive Potential

Contraception

Upon administration of Fosaprepitant for Injection, the efficacy of hormonal contraceptives may be reduced. Advise females of reproductive potential using hormonal contraceptives to use an effective alternative or back-up non-hormonal contraceptive (such as condoms or spermicides) during treatment with Fosaprepitant for Injection and for 1 month following the last dose [see Drug Interactions (7.1), Clinical Pharmacology (12.3)].

8.4 Pediatric Use

This Fosaprepitant for Injection product is not approved for use in pediatric patients.

This Fosaprepitant for Injection product contains 18.8 mg of edetate disodium (EDTA) per vial [see Description (11)]. Edetate disodium is a chelator of metal ions, including calcium. Other fosaprepitant for injection products may contain less edetate disodium.

8.5 Geriatric Use

Of the 1649 adult cancer patients treated with intravenous fosaprepitant in HEC and MEC clinical studies, 27% were aged 65 and over, while 5% were aged 75 and over. Other reported clinical experience has not identified differences in responses between elderly and younger patients. In general, use caution when dosing elderly patients as they have a greater frequency of decreased hepatic, renal or cardiac function and concomitant disease or other drug therapy [see Clinical Pharmacology (12.3)].

8.6 Patients with Hepatic Impairment

The pharmacokinetics of aprepitant in patients with mild and moderate hepatic impairment were similar to those of healthy subjects with normal hepatic function. No dosage adjustment is necessary for patients with mild to moderate hepatic impairment (Child-Pugh score 5 to 9). There are no clinical or pharmacokinetic data in patients with severe hepatic impairment (Child-Pugh score greater than 9). Therefore, additional monitoring for adverse reactions in these patients may be warranted when Fosaprepitant for Injection is administered [see Clinical Pharmacology (12.3)].

10 OVERDOSAGE

There is no specific information on the treatment of overdosage with fosaprepitant or aprepitant.

In the event of overdose, Fosaprepitant for Injection should be discontinued and general supportive treatment and monitoring should be provided. Because of the antiemetic activity of Fosaprepitant for Injection, drug-induced emesis may not be effective in cases of Fosaprepitant for Injection overdosage.

Aprepitant is not removed by hemodialysis.

11 DESCRIPTION

Fosaprepitant for Injection is a sterile, lyophilized formulation containing fosaprepitant dimeglumine, a prodrug of aprepitant, a substance P/neurokinin-1 (NK1) receptor antagonist, an antiemetic agent, chemically described as 1-Deoxy-1-(methylamino)-D-glucitol[3-[[(2R,3S)-2-[(1R)-1-[3,5- bis(trifluoromethyl)phenyl]ethoxy]-3-(4-fluorophenyl)-4-morpholinyl]methyl]-2,5-dihydro-5-oxo-1H-1,2,4- triazol-1-yl]phosphonate (2:1) (salt).

Its empirical formula is C23H22F7N4O6P • 2(C7H17NO5) and its structural formula is:

Fosaprepitant dimeglumine is a white to off-white amorphous powder with a molecular weight of 1004.83. It is freely soluble in water.

Each vial of Fosaprepitant for Injection for administration as an intravenous infusion contains 150 mg of fosaprepitant (equivalent to 245.3 mg of fosaprepitant dimeglumine) and the following inactive ingredients: edetate disodium (18.8 mg), meglumine (75 mg), povidone k12 (600 mg), and water for injection. Hydrochloric acid and/or meglumine may have been added for pH adjustment.

12 CLINICAL PHARMACOLOGY

12.1 Mechanism of Action

Fosaprepitant is a prodrug of aprepitant and accordingly, its antiemetic effects are attributable to aprepitant.

Aprepitant is a selective high-affinity antagonist of human substance P/neurokinin 1 (NK1) receptors. Aprepitant has little or no affinity for serotonin (5-HT3), dopamine, and corticosteroid receptors, the targets of existing therapies for chemotherapy-induced nausea and vomiting (CINV). Aprepitant has been shown in animal models to inhibit emesis induced by cytotoxic chemotherapeutic agents, such as cisplatin, via central actions. Animal and human Positron Emission Tomography (PET) studies with aprepitant have shown that it crosses the blood brain barrier and occupies brain NK1 receptors. Animal and human studies have shown that aprepitant augments the antiemetic activity of the 5-HT3-receptor antagonist ondansetron and the corticosteroid dexamethasone and inhibits both the acute and delayed phases of cisplatin-induced emesis.

12.2 Pharmacodynamics

Cardiac Electrophysiology

In a randomized, double-blind, positive-controlled, thorough QTc study, a single 200-mg dose of fosaprepitant (approximately 1.3 times the recommended dose) had no effect on the QTc interval.

12.3 Pharmacokinetics

Aprepitant after Fosaprepitant Administration

Following administration of a single intravenous 150-mg dose of fosaprepitant, a prodrug of aprepitant administered as a 20-minute infusion to healthy subjects, the mean AUC0-∞ of aprepitant was 37.4 (± 14.8) mcg•hr/mL and the mean maximal aprepitant concentration (Cmax) was 4.2 (± 1.2) mcg/mL. Plasma concentrations of fosaprepitant are below the limits of quantification (10 ng/mL) within 30 minutes of the completion of infusion.

Distribution

Aprepitant is greater than 95% bound to plasma proteins. The mean apparent volume of distribution at steady state (Vdss) was approximately 70 L in humans.

Aprepitant crosses the blood brain barrier in humans [see Clinical Pharmacology (12.1)].

Elimination

Metabolism

Fosaprepitant is converted to aprepitant in in vitro incubations with human liver preparations and in S9 preparations from multiple other human tissues including kidney, lung and ileum. Thus, it appears that the conversion of fosaprepitant to aprepitant can occur in multiple extrahepatic tissues in addition to the liver.

Aprepitant undergoes extensive metabolism. In vitro studies using human liver microsomes indicate that aprepitant is metabolized primarily by CYP3A4 with minor metabolism by CYP1A2 and CYP2C19. Metabolism is largely via oxidation at the morpholine ring and its side chains. No metabolism by CYP2D6, CYP2C9, or CYP2E1 was detected.

In healthy young adults, aprepitant accounts for approximately 24% of the radioactivity in plasma over 72 hours following a single oral 300-mg dose of [^14C]-aprepitant, indicating a substantial presence of metabolites in the plasma. Seven metabolites of aprepitant, which are only weakly active, have been identified in human plasma.

Excretion

Following administration of a single intravenous 100-mg dose of [^14C]-fosaprepitant to healthy subjects, 57% of the radioactivity was recovered in urine and 45% in feces.

Aprepitant is eliminated primarily by metabolism; aprepitant is not renally excreted. The apparent terminal half-life ranged from approximately 9 to 13 hours.

Specific Populations

Geriatric Patients

Following oral administration of a single 125-mg dose of aprepitant on Day 1 and 80 mg once daily on Days 2 through 5, the AUC0-24hr of aprepitant was 21% higher on Day 1 and 36% higher on Day 5 in elderly (65 years and older) relative to younger adults. The Cmax was 10% higher on Day 1 and 24% higher on Day 5 in elderly relative to younger adults. These differences are not considered clinically meaningful [see Use in Specific Populations (8.5)].

Male and Female Patients

Following oral administration of a single dose of aprepitant, ranging from 40 mg to 375 mg, the AUC0-24hr and Cmax are 9% and 17% higher in females as compared with males. The half-life of aprepitant is approximately 25% lower in females as compared with males and Tmax occurs at approximately the same time. These differences are not considered clinically meaningful.

Racial or Ethnic Groups

Following oral administration of a single dose of aprepitant, ranging from 40 mg to 375 mg, the AUC0-24hr and Cmax are approximately 27% and 19% higher in Hispanics as compared with Caucasians. The AUC0-24hr and Cmax were 74% and 47% higher in Asians as compared to Caucasians. There was no difference in AUC0-24hr or Cmax between Caucasians and Blacks. These differences are not considered clinically meaningful.

Patients with Renal Impairment

A single 240-mg oral dose of aprepitant was administered to patients with severe renal impairment (creatinine clearance less than 30 mL/min/1.73 m^2 as measured by 24-hour urinary creatinine clearance) and to patients with end stage renal disease (ESRD) requiring hemodialysis.

In patients with severe renal impairment, the AUC0-∞ of total aprepitant (unbound and protein bound) decreased by 21% and Cmax decreased by 32%, relative to healthy subjects (creatinine clearance greater than 80 mL/min estimated by Cockcroft-Gault method). In patients with ESRD undergoing hemodialysis, the AUC0-∞ of total aprepitant decreased by 42% and Cmax decreased by 32%. Due to modest decreases in protein binding of aprepitant in patients with renal disease, the AUC of pharmacologically active unbound drug was not significantly affected in patients with renal impairment compared with healthy subjects. Hemodialysis conducted 4 or 48 hours after dosing had no significant effect on the pharmacokinetics of aprepitant; less than 0.2% of the dose was recovered in the dialysate.

Patients with Hepatic Impairment

Fosaprepitant is metabolized in various extrahepatic tissues; therefore hepatic impairment is not expected to alter the conversion of fosaprepitant to aprepitant.

Following administration of a single 125-mg oral dose of aprepitant on Day 1 and 80 mg once daily on Days 2 and 3 to patients with mild hepatic impairment (Child-Pugh score 5 to 6), the AUC0-24hr of aprepitant was 11% lower on Day 1 and 36% lower on Day 3, as compared with healthy subjects given the same regimen. In patients with moderate hepatic impairment (Child-Pugh score 7 to 9), the AUC0-24hr of aprepitant was 10% higher on Day 1 and 18% higher on Day 3, as compared with healthy subjects given the same regimen. These differences in AUC0-24hr are not considered clinically meaningful. There are no clinical or pharmacokinetic data in patients with severe hepatic impairment (Child-Pugh score greater than 9) [see Use in Specific Populations (8.6)].

Body Mass Index (BMI)

For every 5 kg/m^2 increase in BMI, AUC0-24hr and Cmax of aprepitant decrease by 9% and 10%. BMI of subjects in the analysis ranged from 18 kg/m^2 to 36 kg/m^2. This change is not considered clinically meaningful.

Drug Interactions Studies

Fosaprepitant, given as a single 150-mg dose, is a weak inhibitor of CYP3A4, with no evidence of inhibition or induction of CYP3A4 observed on Day 4. The weak inhibition of CYP3A4 continues for 2 days after single dose administration of fosaprepitant. Aprepitant is a substrate, an inhibitor, and an inducer of CYP3A4. Aprepitant is also an inducer of CYP2C9.

Fosaprepitant or aprepitant is unlikely to interact with drugs that are substrates for the P-glycoprotein transporter.

Effects of Fosaprepitant/Aprepitant on the Pharmacokinetics of Other Drugs

CYP3A4 Substrates

Midazolam: Fosaprepitant 150 mg administered as a single intravenous dose on Day 1 increased the AUC0-∞ of midazolam by approximately 1.8-fold on Day 1 and had no effect on Day 4 when midazolam was coadministered as a single oral dose of 2 mg on Days 1 and 4 [see Drug Interactions (7.1)].

Corticosteroids:

Dexamethasone: Fosaprepitant administered as a single 150 mg intravenous dose on Day 1 increased the AUC0-24hr of dexamethasone, administered as a single 8-mg oral dose on Days 1, 2, and 3, by approximately 2-fold on Days 1 and 2 [see Dosage and Administration (2.1), Drug Interactions (7.1)].

Methylprednisolone: When oral aprepitant as a 3-day regimen (125-mg/80-mg/80-mg) was administered with intravenous methylprednisolone 125 mg on Day 1 and oral methylprednisolone 40 mg on Days 2 and 3, the AUC of methylprednisolone was increased by 1.34-fold on Day 1 and by 2.5-fold on Day 3 [see Drug Interactions (7.1)].

Chemotherapeutic agents:

Docetaxel: In a pharmacokinetic study, oral aprepitant administered as a 3-day regimen (125-mg/80-mg/80-mg) did not influence the pharmacokinetics of docetaxel.

Vinorelbine: In a pharmacokinetic study, oral aprepitant administered as a 3-day regimen (125-mg/80-mg/80-mg) did not influence the pharmacokinetics of vinorelbine to a clinically significant degree.

Oral contraceptives: When oral aprepitant was administered as a 3-day regimen (125-mg/80-mg/80-mg) with ondansetron and dexamethasone, and coadministered with an oral contraceptive containing ethinyl estradiol and norethindrone, the trough concentrations of both ethinyl estradiol and norethindrone were reduced by as much as 64% for 3 weeks post-treatment [see Drug Interactions (7.1)].

CYP2C9 substrates (Warfarin, Tolbutamide):

Warfarin: A single 125-mg dose of oral aprepitant was administered on Day 1 and 80 mg/day on Days 2 and 3 to subjects who were stabilized on chronic warfarin therapy. Although there was no effect of oral aprepitant on the plasma AUC of R(+) or S(-) warfarin determined on Day 3, there was a 34% decrease in S(-) warfarin trough concentration accompanied by a 14% decrease in the prothrombin time (reported as International Normalized Ratio or INR) 5 days after completion of dosing with oral aprepitant [see Drug Interactions (7.1)].

Tolbutamide: Oral aprepitant, when given as 125 mg on Day 1 and 80 mg/day on Days 2 and 3, decreased the AUC of tolbutamide by 23% on Day 4, 28% on Day 8, and 15% on Day 15, when a single dose of tolbutamide 500 mg was administered prior to the administration of the 3-day regimen of oral aprepitant and on Days 4, 8, and 15. This effect was not considered clinically important.

Other Drugs

P-glycoprotein substrates: Aprepitant is unlikely to interact with drugs that are substrates for the P-glycoprotein transporter, as demonstrated by the lack of interaction of oral aprepitant with digoxin in a clinical drug interaction study.

5-HT3 antagonists: In clinical drug interaction studies, aprepitant did not have clinically important effects on the pharmacokinetics of ondansetron, granisetron, or hydrodolasetron (the active metabolite of dolasetron).

Effect of Other Drugs on the Pharmacokinetics of Fosaprepitant/Aprepitant

Rifampin: When a single 375-mg dose of oral aprepitant was administered on Day 9 of a 14-day regimen of
600 mg/day of rifampin, a strong CYP3A4 inducer, the AUC of aprepitant decreased approximately 11-fold and the mean terminal half-life decreased approximately 3-fold [see Drug Interactions (7.2)].

Ketoconazole: When a single 125-mg dose of oral aprepitant was administered on Day 5 of a 10-day regimen of 400 mg/day of ketoconazole, a strong CYP3A4 inhibitor, the AUC of aprepitant increased approximately 5-fold and the mean terminal half-life of aprepitant increased approximately 3-fold [see Drug Interactions (7.2)].

Diltiazem: In a study in 10 patients with mild to moderate hypertension, administration of 100 mg of fosaprepitant as an intravenous infusion with 120 mg of diltiazem, a moderate CYP3A4 inhibitor administered three times daily, resulted in a 1.5-fold increase in the aprepitant AUC and a 1.4-fold increase in the diltiazem AUC.

When fosaprepitant was administered with diltiazem, the mean maximum decrease in diastolic blood pressure was significantly greater than that observed with diltiazem alone [24.3 ± 10.2 mm Hg with fosaprepitant versus 15.6 ± 4.1 mm Hg without fosaprepitant]. The mean maximum decrease in systolic blood pressure was also greater after co-administration of diltiazem with fosaprepitant than administration of diltiazem alone [29.5 ± 7.9 mm Hg with fosaprepitant versus 23.8 ± 4.8 mm Hg without fosaprepitant]. Coadministration of fosaprepitant and diltiazem; however, did not result in any additional clinically significant changes in heart rate or PR interval, beyond those changes observed with diltiazem alone [see Drug Interactions (7.2)].

Paroxetine: Coadministration of once daily doses of oral aprepitant 170 mg, with paroxetine 20 mg once daily, resulted in a decrease in AUC by approximately 25% and Cmax by approximately 20% of both aprepitant and paroxetine. This effect was not considered clinically important.

13 NONCLINICAL TOXICOLOGY

13.1 Carcinogenesis, Mutagenesis, Impairment of Fertility

Carcinogenesis

Carcinogenicity studies were conducted in Sprague-Dawley rats and in CD-1 mice for 2 years. In the rat carcinogenicity studies, animals were treated with oral doses ranging from 0.05 to 1,000 mg/kg twice daily. The highest dose produced systemic exposures to aprepitant approximately equivalent to (female rats) or less than (male rats) the adult human exposure at the RHD of 150 mg. Treatment with aprepitant at doses of 5 to 1,000 mg/kg twice daily caused an increase in the incidences of thyroid follicular cell adenomas and carcinomas in male rats. In female rats, it produced hepatocellular adenomas at 5 to 1,000 mg/kg twice daily and hepatocellular carcinomas and thyroid follicular cell adenomas at 125 to 1,000 mg/kg twice daily. In the mouse carcinogenicity studies, the animals were treated with oral doses ranging from 2.5 to 2,000 mg/kg/day. The highest dose produced a systemic exposure approximately 2 times the adult human exposure at the RHD of 150 mg. Treatment with aprepitant produced skin fibrosarcomas at 125 and 500 mg/kg/day doses in male mice. Carcinogenicity studies were not conducted with fosaprepitant.

Mutagenesis

Aprepitant and fosaprepitant were not genotoxic in the Ames test, the human lymphoblastoid cell (TK6) mutagenesis test, the rat hepatocyte DNA strand break test, the Chinese hamster ovary (CHO) cell chromosome aberration test and the mouse micronucleus test.

Impairment of Fertility

Fosaprepitant, when administered intravenously, is rapidly converted to aprepitant. In the fertility studies conducted with fosaprepitant and aprepitant, the highest systemic exposures to aprepitant were obtained following oral administration of aprepitant. Oral aprepitant did not affect the fertility or general reproductive performance of male or female rats at doses up to the maximum feasible dose of 1,000 mg/kg twice daily (providing exposure in male rats lower than the exposure at the recommended adult human dose of 150 mg and exposure in female rats approximately equivalent to the adult human exposure).

14 CLINICAL STUDIES

The safety and efficacy of Fosaprepitant for Injection have been established based on adequate and well-controlled adult studies of another intravenous fosaprepitant product in chemotherapy induced nausea and vomiting. Below is a display of the results of these adequate and well-controlled studies of fosaprepitant in these conditions.

14.1 Prevention of Nausea and Vomiting Associated with HEC in Adults

In a randomized, parallel, double-blind, active-controlled study, 150 mg fosaprepitant as a single intravenous infusion (N=1147) was compared to a 3-day oral aprepitant capsules regimen (N=1175) in patients receiving a HEC regimen that included cisplatin (≥70 mg/m^2). All patients in both groups received dexamethasone and ondansetron (see Table 11). Patient demographics were similar between the two treatment groups. Of the total 2322 patients, 63% were men, 56% White, 26% Asian, 3% American Indian/Alaska Native, 2% Black, 13% Multi-Racial, and 33% Hispanic/Latino ethnicity. Patient ages ranged from 19 to 86 years of age, with a mean age of 56 years. Other concomitant chemotherapy agents commonly administered were fluorouracil (17%), gemcitabine (16%), paclitaxel (15%), and etoposide (12%).

Table 11 Treatment Regimens in Adult HEC Trial*
 | Day 1 | Day 2 | Day 3 | Day 4
Intravenous Fosaprepitant Regimen
Fosaprepitant | 150 mg intravenously over 20 to 30 minutes approximately 30 minutes prior to chemotherapy | none | none | none
Oral dexamethasone† | 12 mg | 8 mg | 8 mg twice daily | 8 mg twice daily
Ondansetron | Ondansetron‡ | none | none | none
Oral Aprepitant Regimen
Aprepitant capsules | 125 mg | 80 mg | 80 mg | none
Oral dexamethasone§ | 12 mg | 8 mg | 8 mg | 8 mg
Ondansetron | Ondansetron‡ | none | none | none
*Fosaprepitant placebo, aprepitant capsules placebo and dexamethasone placebo (in the evenings on Days 3 and 4) were used to maintain blinding.
†Dexamethasone was administered 30 minutes prior to chemotherapy treatment on Day 1 and in the morning on Days 2 through 4. Dexamethasone was also administered in the evenings on Days 3 and 4. The 12 mg dose of dexamethasone on Day 1 and the 8 mg once daily dose on Day 2 reflects a dosage adjustment to account for a drug interaction with the fosaprepitant regimen [see Clinical Pharmacology (12.3)].
‡Ondansetron 32 mg intravenous was used in the clinical trials of fosaprepitant. Although this dose was used in clinical trials, this is no longer the currently recommended dose. Refer to the ondansetron prescribing information for the current recommended dose.
§Dexamethasone was administered 30 minutes prior to chemotherapy treatment on Day 1 and in the morning on Days 2 through 4. The 12 mg dose of dexamethasone on Day 1 and the 8 mg once daily dose on Days 2 through 4 reflects a dosage adjustment to account for a drug interaction with the oral aprepitant capsules regimen [see Clinical Pharmacology (12.3)].

The efficacy of a single-dose of intravenous fosaprepitant was evaluated based on the primary and secondary endpoints listed in Table 12 and was shown to be non-inferior to that of the 3-day oral aprepitant regimen with regard to complete response in each of the evaluated phases. The pre-specified non-inferiority margin for complete response in the overall phase was 7%. The pre-specified non-inferiority margin for complete response in the delayed phase was 7.3%. The pre-specified non-inferiority margin for no vomiting in the overall phase was 8.2%.

Table 12 Percent of Adult Patients Receiving HEC Responding by Treatment Group and Phase - Cycle 1
ENDPOINTS | Intravenous Fosaprepitant Regimen | Oral Aprepitant Regimen | Difference†
 | (N=1106)* | (N=1134)* | (95% CI)
 | % | %
PRIMARY ENDPOINT
Complete Response‡
Overall§ | 71.9 | 72.3 | -0.4 (-4.1, 3.3)
SECONDARY ENDPOINTS
Complete Response‡
Delayed phase¶ | 74.3 | 74.2 | 0.1 (-3.5, 3.7)
No Vomiting
Overall§ | 72.9 | 74.6 | -1.7 (-5.3, 2.0)
*N: Number of patients included in the primary analysis of complete response.
†Difference and Confidence interval (CI) were calculated using the method proposed by Miettinen and Nurminen and adjusted for Gender.
‡Complete Response = no vomiting and no use of rescue therapy.
§Overall = 0 to 120 hours post-initiation of cisplatin chemotherapy.
¶Delayed phase = 25 to 120 hours post-initiation of cisplatin chemotherapy.

14.2 Prevention of Nausea and Vomiting Associated with MEC in Adults

In a randomized, parallel, double-blind, active comparator-controlled study, fosaprepitant 150 mg as a single intravenous infusion (N=502) in combination with ondansetron and dexamethasone (intravenous fosaprepitant regimen) was compared with ondansetron and dexamethasone alone (standard therapy) (N=498) (see Table 13) in patients receiving a MEC regimen. Patient demographics were similar between the two treatment groups. Of the total 1,000 patients included in the efficacy analysis, 41% were men, 84% White, 4% Asian, 1% American Indian/Alaska Native, 2% Black, 10% Multi-Racial, and 19% Hispanic/Latino ethnicity. Patient ages ranged from 23 to 88 years of age, with a mean age of 60 years. The most commonly administered MEC chemotherapeutic agents were carboplatin (51%), oxaliplatin (24%), and cyclophosphamide (12%).

Table 13 Treatment Regimens in Adult MEC Trial*
 | Day 1 | Day 2 | Day 3
Intravenous Fosaprepitant Regimen
Fosaprepitant | 150 mg intravenously over 20 to 30 minutes approximately 30 minutes prior to chemotherapy | none | none
Oral Dexamethasone† | 12 mg | none | none
Oral Ondansetron‡ | 8 mg for 2 doses | none | none
Standard Therapy
Oral Dexamethasone | 20 mg | none | none
Oral Ondansetron‡ | 8 mg for 2 doses | 8 mg twice daily | 8 mg twice daily
* Fosaprepitant placebo and dexamethasone placebo (on Day 1) were used to maintain blinding.
†Dexamethasone was administered 30 minutes prior to chemotherapy treatment on Day 1. The 12 mg dose reflects a dosage adjustment to account for a drug interaction with the fosaprepitant regimen [see Clinical Pharmacology (12.3)].
‡The first ondansetron dose was administered 30 to 60 minutes prior to chemotherapy treatment on Day 1 and the second dose was administered 8 hours after first ondansetron dose.

The primary endpoint was complete response (defined as no vomiting and no rescue therapy) in the delayed phase (25 to 120 hours) of chemotherapy-induced nausea and vomiting. The results by treatment group are shown in Table 14.

Table 14 Percent of Adult Patients Receiving MEC Responding by Treatment Group
ENDPOINTS | Intravenous Fosaprepitant Regimen | Standard Therapy Regimen | P-Value | Treatment Difference (95% CI)
 | (N=502)* | (N=498)*
 | % | %
PRIMARY ENDPOINT
Complete Response†
Delayed phase‡ | 78.9 | 68.5 | <0.001 | 10.4 (5.1, 15.9)
*N: Number of patients included in the intention to treat population.
†Complete Response = no vomiting and no use of rescue therapy.
‡Delayed phase = 25 to 120 hours post-initiation of chemotherapy.

16 HOW SUPPLIED/STORAGE AND HANDLING

Fosaprepitant for Injection is available as follows:

One single-dose glass vial containing 150 mg fosaprepitant as a sterile, white to off-white lyophilized powder for reconstitution. Supplied as follows:

NDC 0591-4385-79 1 vial per carton.

Storage

Store at 2° to 8°C (36° to 46°F).

For storage of reconstituted drug solution see Dosage and Administration 2.2.

17 PATIENT COUNSELING INFORMATION

Advise the patient to read the FDA-approved patient labeling (Patient Information).

Hypersensitivity

Advise patients that hypersensitivity reactions, including anaphylaxis and anaphylactic shock, have been reported in patients taking fosaprepitant. Advise patients to seek immediate medical attention if they experience signs or symptoms of a hypersensitivity reaction, such as hives, rash and itching, skin peeling or sores, flushing, difficulty in breathing or swallowing, or dizziness, rapid or weak heartbeat or feeling faint [see Warnings and Precautions (5.2)].

Infusion Site Reactions

Advise patients to seek medical attention if they experience new or worsening signs or symptoms of an infusion site reaction, such as erythema, edema, pain, necrosis, vasculitis, or thrombophlebitis at or near the infusion site [see Warnings and Precautions (5.3)].

Drug Interactions

Advise patients to discuss all medications they are taking, including other prescription, non-prescription medication or herbal products [see Contraindications (4), Warnings and Precautions (5.1)].

Warfarin: Instruct patients on chronic warfarin therapy to follow instructions from their healthcare provider regarding blood draws to monitor their INR during the 2-week period, particularly at 7 to 10 days, following initiation of Fosaprepitant for Injection with each chemotherapy cycle [see Warnings and Precautions (5.4)].

Hormonal Contraceptives: Advise patients that administration of Fosaprepitant for Injection may reduce the efficacy of hormonal contraceptives. Instruct patients to use effective alternative or back-up methods of contraception (such as condoms or spermicides) during treatment with Fosaprepitant for Injection and for 1 month following administration of Fosaprepitant for Injection [see Warnings and Precautions (5.5), Use in Specific Populations (8.3)].

Manufactured in Romania By:
Sindan Pharma SRL
11 Ion Mihalache Blvd.
Bucharest 1, Romania 011171

Manufactured For:
Teva Pharmaceuticals
Parsippany, NJ 07054

PATIENT INFORMATION
FOSAPREPITANT for injection (FOS a PRE pi tant)
for intravenous use

What is Fosaprepitant for Injection?

Fosaprepitant for Injection is a prescription medicine used with other medicines that treat nausea and vomiting in adults to prevent nausea and vomiting caused by certain anti-cancer (chemotherapy) medicines.

- Fosaprepitant for Injection is not used to treat nausea and vomiting that you already have.
- It is not known if Fosaprepitant for Injection is safe and effective in children.

Do not receive Fosaprepitant for Injection if you:

- are allergic to fosaprepitant, aprepitant, or any of the ingredients in Fosaprepitant for Injection. See the end of this leaflet for a complete list of the ingredients in Fosaprepitant for Injection.
- are taking pimozide (ORAP).

Before receiving Fosaprepitant for Injection, tell your healthcare provider about all your medical conditions including, if you:

- have liver problems.
- are pregnant or plan to become pregnant. It is not known if Fosaprepitant for Injection can harm your unborn baby.
  - Women who use birth control medicines containing hormones to prevent pregnancy (birth control pills, skin patches, implants, and certain IUDs) should also use a backup method of birth control that does not contain hormones, such as condoms or spermicides, during treatment with Fosaprepitant for Injection and for 1 month after receiving the last dose of Fosaprepitant for Injection.
- are breastfeeding or plan to breastfeed. It is not known if Fosaprepitant for Injection passes into your breast milk. Talk to your healthcare provider about the best way to feed your baby if you receive Fosaprepitant for Injection.

Tell your healthcare provider about all the medicines you take, including prescription and over-the-counter medicines, vitamins, and herbal supplements.

Fosaprepitant for Injection may affect the way other medicines work, and other medicines may affect the way Fosaprepitant for Injection works , causing serious side effects.

Know the medicines you take. Keep a list of them to show your healthcare provider or pharmacist when you get a new medicine.

How will I receive Fosaprepitant for Injection?

Fosaprepitant for Injection will be given on Day 1 of chemotherapy treatment. It will be given to you by intravenous (IV) infusion in your vein about 50 to 60 minutes before you start your chemotherapy treatment.

If you take the blood thinner medicine warfarin sodium (COUMADIN, JANTOVEN), your healthcare provider may do blood tests after you receive Fosaprepitant for Injection to check your blood clotting.

What are the possible side effects of Fosaprepitant for Injection?

Fosaprepitant for Injection may cause serious side effects, including:

- Serious allergic reactions. Allergic reactions can happen with Fosaprepitant for Injection and may be serious. Tell your healthcare provider or nurse right away if you have hives, rash, itching, flushing or redness of your face or skin, trouble breathing or swallowing, dizziness, a rapid or weak heartbeat, or you feel faint during or soon after you receive Fosaprepitant for Injection, as you may need emergency medical care.
- Severe skin reactions, which may include rash, skin peeling, or sores, may occur. Get medical care right away if you have signs of a severe skin reaction.

- Infusion site reactions (ISR) at or near the infusion site have happened with Fosaprepitant for Injection.

Most severe ISR have happened with a certain type of chemotherapy medicine that can burn or blister your skin (vesicant) with side effects, including pain, swelling and redness. Death of skin tissue (necrosis) has happened in some people getting this type of chemotherapy medicine. Most ISR can happen with the first, second, or third dose and some can last up to 2 weeks or longer. Tell your healthcare provider right away if you get any infusion site side effects.

The most common side effects of Fosaprepitant for Injection include:

- tiredness

- feeling weak or numb in your arms and legs

- diarrhea

- indigestion or heartburn

- low white blood cell and red blood cell counts

- urinary tract infection

- weakness

- pain in your arms and legs

Tell your healthcare provider if you have any side effect that bothers you or that does not go away. These are not all of the possible side effects of Fosaprepitant for Injection. Call your doctor for medical advice about side effects. You may report side effects to FDA at 1-800-FDA-1088.

General information about the safe and effective use of Fosaprepitant for Injection.

If you would like more information about Fosaprepitant for Injection, talk with your healthcare provider. You can ask your healthcare provider or pharmacist for information about Fosaprepitant for Injection that is written for health professionals. For more information about Fosaprepitant for Injection call Teva at 1-888-838-2872.

What are the ingredients in Fosaprepitant for Injection?

Active ingredient: fosaprepitant dimeglumine

Inactive ingredients: edetate disodium, meglumine, povidone k12, and water for injection. Hydrochloric acid and/or meglumine may have been added for pH adjustment.

Brands listed are trademarks of their respective owners.

Manufactured in Romania By: Sindan Pharma SRL, 11th Ion Mihalache Blvd., Bucharest 1, Romania 011171
Manufactured For: Teva Pharmaceuticals, Parsippany, NJ 07054

This Patient Information has been approved by the U.S. Food and Drug Administration. Rev. A 6/2022

PRINCIPAL DISPLAY PANEL

NDC 0591-4385-79

Fosaprepitant for Injection
150 mg/vial

Sterile Lyophilized Powder for Intravenous Use Only After Reconstitution and Dilution

DO NOT USE WITH SOLUTIONS CONTAINING DIVALENT CATIONS (e.g., Ca^2+, Mg^2+) INCLUDING LACTATED RINGER’S SOLUTION AND HARTMANN’S SOLUTION.

Each vial contains:
Fosaprepitant…………….150 mg
(equivalent to 245.3 mg of fosaprepitant dimeglumine)

Rx only

Single-Dose Vial
Discard Unused Portion